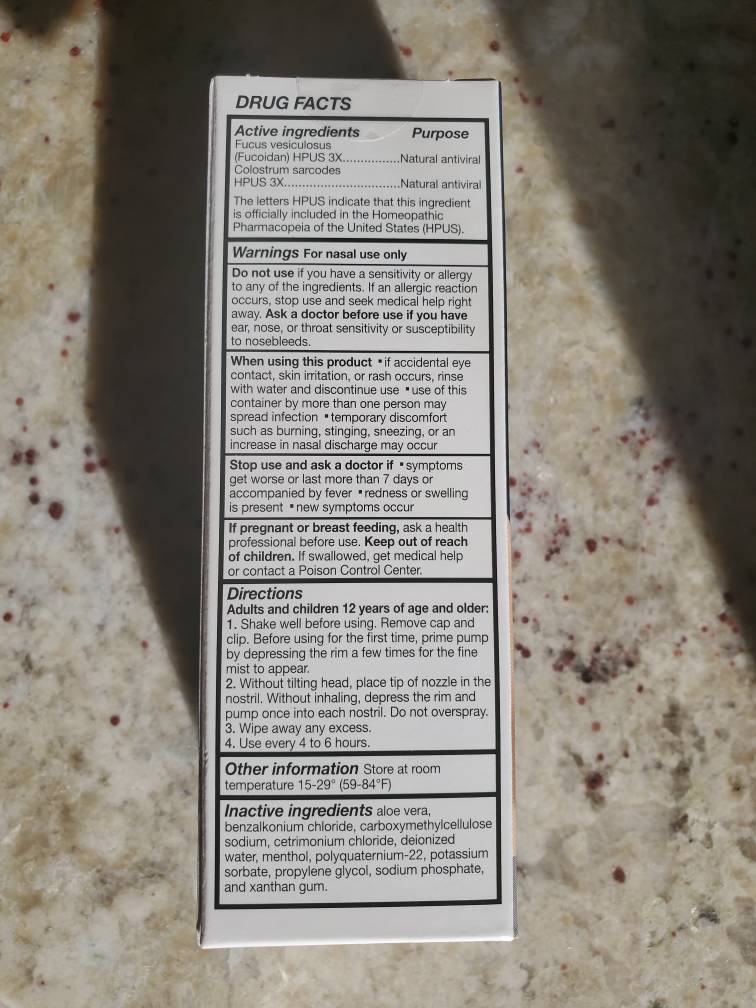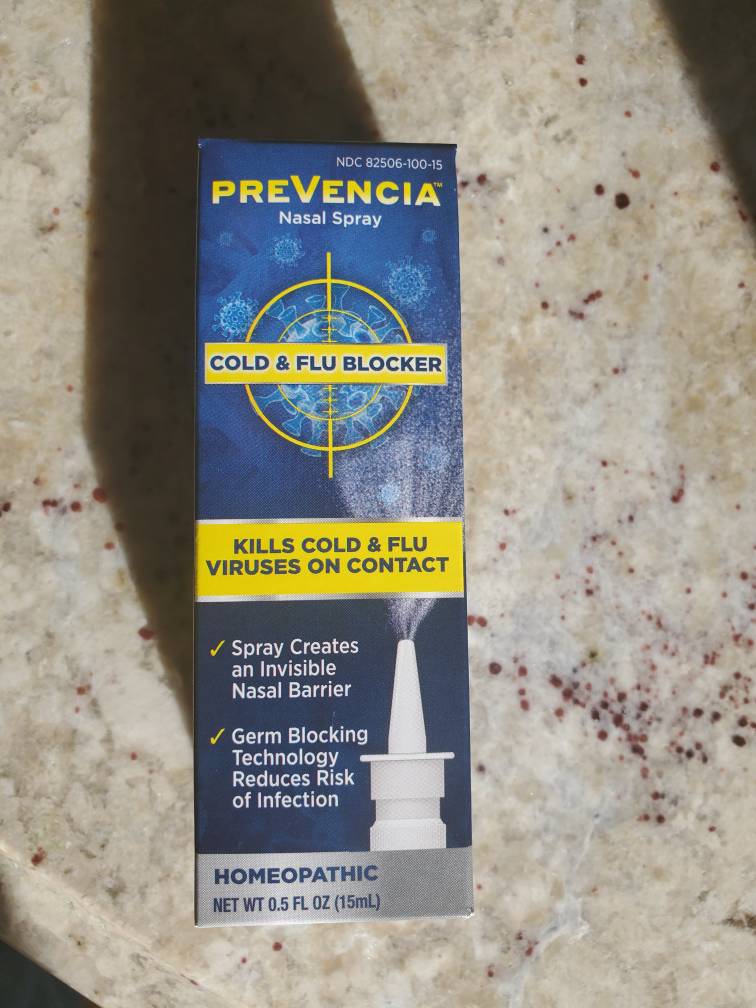 DRUG LABEL: PREVENCIA
NDC: 82506-100 | Form: SPRAY
Manufacturer: Core Consumer Healthcare LLC
Category: homeopathic | Type: HUMAN OTC DRUG LABEL
Date: 20221011

ACTIVE INGREDIENTS: FUCUS VESICULOSUS 0.015 mg/15 mL; BOS TAURUS COLOSTRUM 0.015 mg/15 mL
INACTIVE INGREDIENTS: BENZALKONIUM CHLORIDE 0.15 mL/15 mL

Prevencia Nasal Spray

Drug Facts Labeling

Drug Facts

Active ingredients Purpose

Fucus vesiculosus (Fucoidan) HPUS 3X Natural antiviral

Colostrum sarcodes HPUS 3X Natural antiviral

The letters HPUS indicate that this ingredient is officially included in the Homeopathic Pharmacopeia of the United States (HPUS).

Warnings

For nasal use only

Do not use if you have a sensitivity or allergy to any of the ingredients. If an allergic reaction occurs, stop use and seek medical help right away.

Ask a doctor before use if you have ear, nose, or throat sensitivity or susceptibility to nosebleeds.

When using this product

if accidental eye contact, skin irritation, or rash occurs, rinse with water and discontinue use
use of this container by more than one person may spread infection
temporary discomfort such as burning, stinging, sneezing, or an increase in nasal discharge may occur

Stop use and ask a doctor if

symptoms get worse or last more than 7 days or accompanied by fever
redness or swelling is present * new symptoms occur

If pregnant or breast feeding, ask a health professional before use.

Keep out of reach of children. If swallowed, get medical help or contact a Poison Control Center.

Directions

Adults and children 12 years of age and older:

Shake well before using. Remove cap and clip. Before using for the first time, prime pump by depressing the rim a few times for the fine mist to appear.
Without tilting head, place tip of nozzle in the nostril. Without inhaling, depress the rim and pump once into each nostril. Do not overspray.
Wipe away any excess.
Use every 4 to 6 hours.

Other information * store at room temperature 15-29° (59-84°F)

Inactive ingredients aloe vera, benzalkonium chloride, carboxymethylcellulose sodium, cetrimonium chloride, deionized water, menthol, polyquaternium-22, potassium sorbate, propylene glycol, sodium phosphate, and xanthan gum.

Directions for Use

Directions

Adults and children 12 years of age and older:

Shake well before using. Remove cap and clip. Before using for the first time, prime pump by depressing the rim a few times for the fine mist to appear.
Without tilting head, place tip of nozzle in the nostril. Without inhaling, depress the rim and pump once into each nostril. Do not overspray.
Wipe away any excess.
Use every 4 to 6 hours.

Warnings

For nasal use only

Do not use if you have a sensitivity or allergy to any of the ingredients. If an allergic reaction occurs, stop use and seek medical help right away.

Ask a doctor before use if you have ear, nose, or throat sensitivity or susceptibility to nosebleeds.

When using this product

if accidental eye contact, skin irritation, or rash occurs, rinse with water and discontinue use
use of this container by more than one person may spread infection
temporary discomfort such as burning, stinging, sneezing, or an increase in nasal discharge may occur

Stop use and ask a doctor if

symptoms get worse or last more than 7 days or accompanied by fever
redness or swelling is present * new symptoms occur

If pregnant or breast feeding, ask a health professional before use.

Keep out of reach of children. If swallowed, get medical help or contact a Poison Control Center.

Inactive Ingredients

Inactive ingredients aloe vera, benzalkonium chloride, carboxymethylcellulose sodium, cetrimonium chloride, deionized water, menthol, polyquaternium-22, potassium sorbate, propylene glycol, sodium phosphate, and xanthan gum.

Indications and Usage

Use to reduce risk of cold and flu infections

Keep out of reach of children. If swallowed, get medical help or contact a Poison Control Center.

OTC Purpose

Reduce risk of cold and flu infections